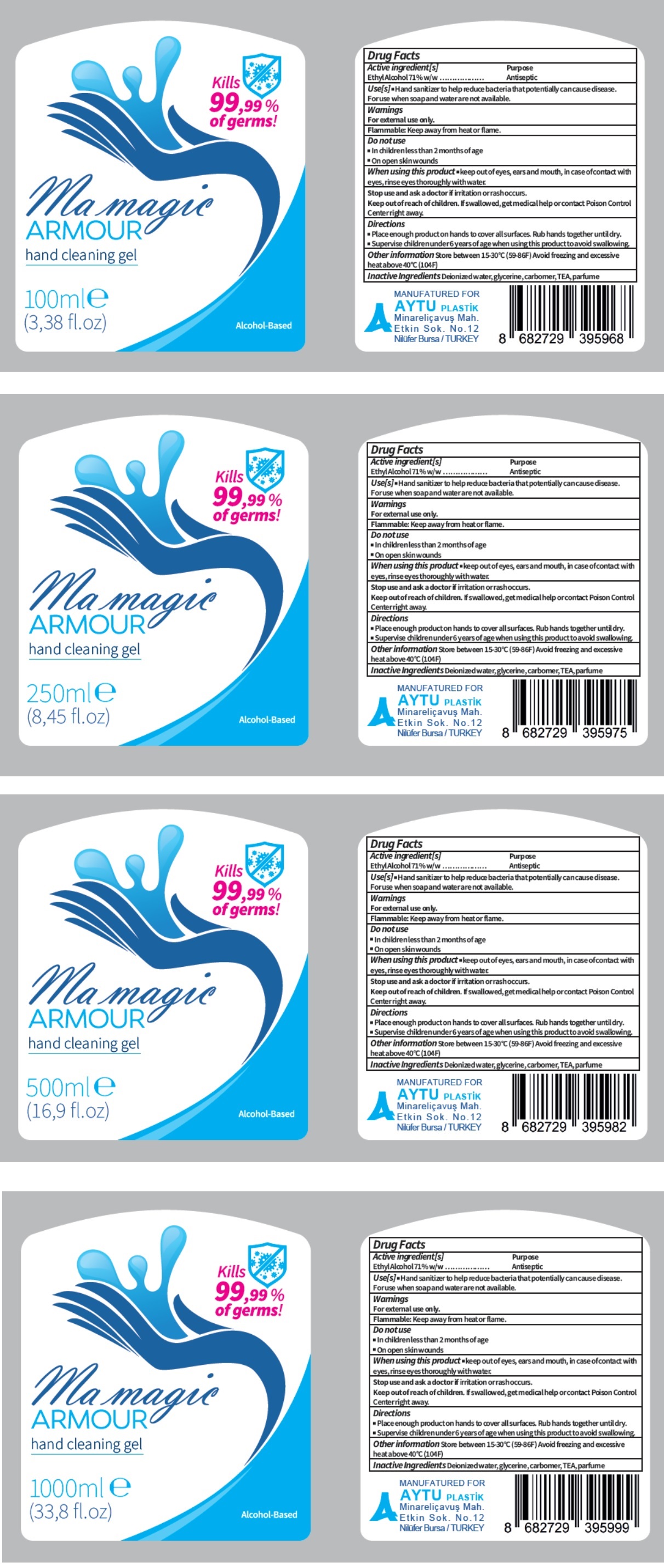 DRUG LABEL: Ma magic ARMOUR
NDC: 78373-002 | Form: GEL
Manufacturer: Ay-tu Plastik Ambalaj Sanayi Ve Ticaret Limited Sirketi
Category: otc | Type: HUMAN OTC DRUG LABEL
Date: 20200601

ACTIVE INGREDIENTS: ALCOHOL 0.71 mL/1 mL
INACTIVE INGREDIENTS: WATER; GLYCERIN; CARBOMER HOMOPOLYMER, UNSPECIFIED TYPE; TEA LEAF

Ma magic ARMOUR hand cleaning gel

Active ingredient[s]

Ethyl Alcohol 71% w/w

Purpose

Antiseptic

Use[s]

■ Hand sanitizer to help reduce bacteria that potentially can cause disease. For use when soap and water are not available.

Warnings

For external use only.

Flammable: Keep away from heat or flame.

Do not use

■ In children less than 2 months of age

■ On open skin wounds

When using this product ■ keep out of eyes, ears, and mouth, in case of contact with eyes, rinse eyes thoroughly with water.

Stop use and ask a doctor if irritation or rash occurs.

Keep out of reach of children. If swallowed, get medical help or contact Poison Control Center right away.

Directions

■ Place enough product on hands to cover all surfaces. Rub hands together until dry.
■ Supervise children under 6 years of age when using this product to avoid swallowing.

Other information

Store between 15-30°C (59-86F) Avoid freezing and excessive heat above 40°C (104F)

Inactive Ingredients

Deionized water, glycerine, carbomer, TEA, parfume

Kills 99,99% of germs!

Alcohol-Based

MANUFACTURED FOR
AYTU PLASTİK

Minareliçavuş Mah.

Etkin Sok. No. 12

Nilüfer Bursa / TURKEY